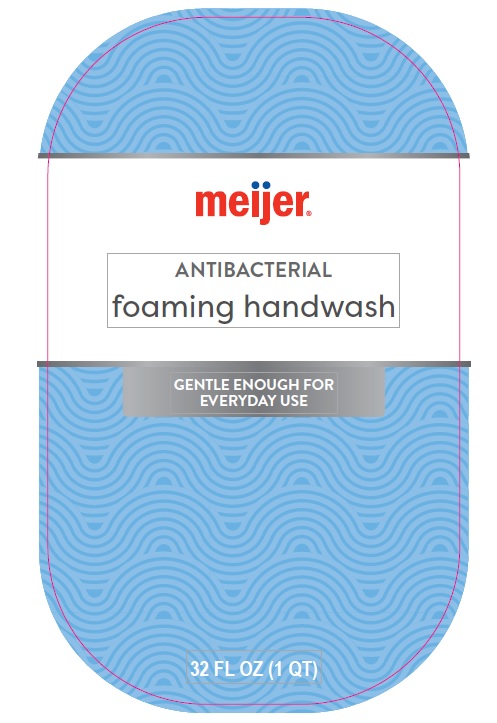 DRUG LABEL: Meijer
NDC: 79481-1013 | Form: SOLUTION
Manufacturer: Meijer
Category: otc | Type: HUMAN OTC DRUG LABEL
Date: 20250328

ACTIVE INGREDIENTS: BENZALKONIUM CHLORIDE 0.13 mg/100 mL
INACTIVE INGREDIENTS: GLYCERIN; FD&C BLUE NO. 1; D&C RED NO. 33; COCAMIDOPROPYL BETAINE; WATER; LAURAMIDOPROPYLAMINE OXIDE; MYRISTAMIDOPROPYLAMINE OXIDE; PEG-120 METHYL GLUCOSE DIOLEATE; CETRIMONIUM CHLORIDE; METHYLISOTHIAZOLINONE; METHYLCHLOROISOTHIAZOLINONE; EDETATE DISODIUM

Meijer

Active Ingredient

Benzalkonium Chloride 0.13%

Purpose

Antibacterial

Uses

Helps eliminate bacteria on the skin

Warnings

For external rectal use only

When using this product

avoid contact with eyes. If contact occurs, rinse eyes thoroughly with water

Stop using this product and ask a doctor it

irritation and redness develop and lasts

Keep out of reach of children

In case of accidental ingestion, get medical help or contact Poison Control Center immediately

Directions

Dispense onto wet hand. Work into a lather. Rinse well

Inactive Ingredients

Water, Cocamidopropyl Betaine, Lauramidopropylamine Oxide, Myristamidopropylamine Oxide, PEG – 120 Methyl Glucose Dioleate, Cetrimonium Chloride, Glycerin, Citric Acid, Disodium EDTA, Fragrance, Methylisothiazolinone, Methylchloroisothiazolinone, Red 33 (CI17200), Blue 1 (CI42090)

Questions or Comments?

Call toll free 1-800-527-7731

DISTRIBUTED BY

MEIJER DISTRIBUTION INC., GRAND RAPIDS, MI, 49544

www.meijer.com

PACKAGE LABEL

NDC 79481-1013-2

Meijer ANTIBACTERIAL foaming handwash

GENTLE ENOUGH FOR EVERYDAY USE

32 FL OZ (1 QT)